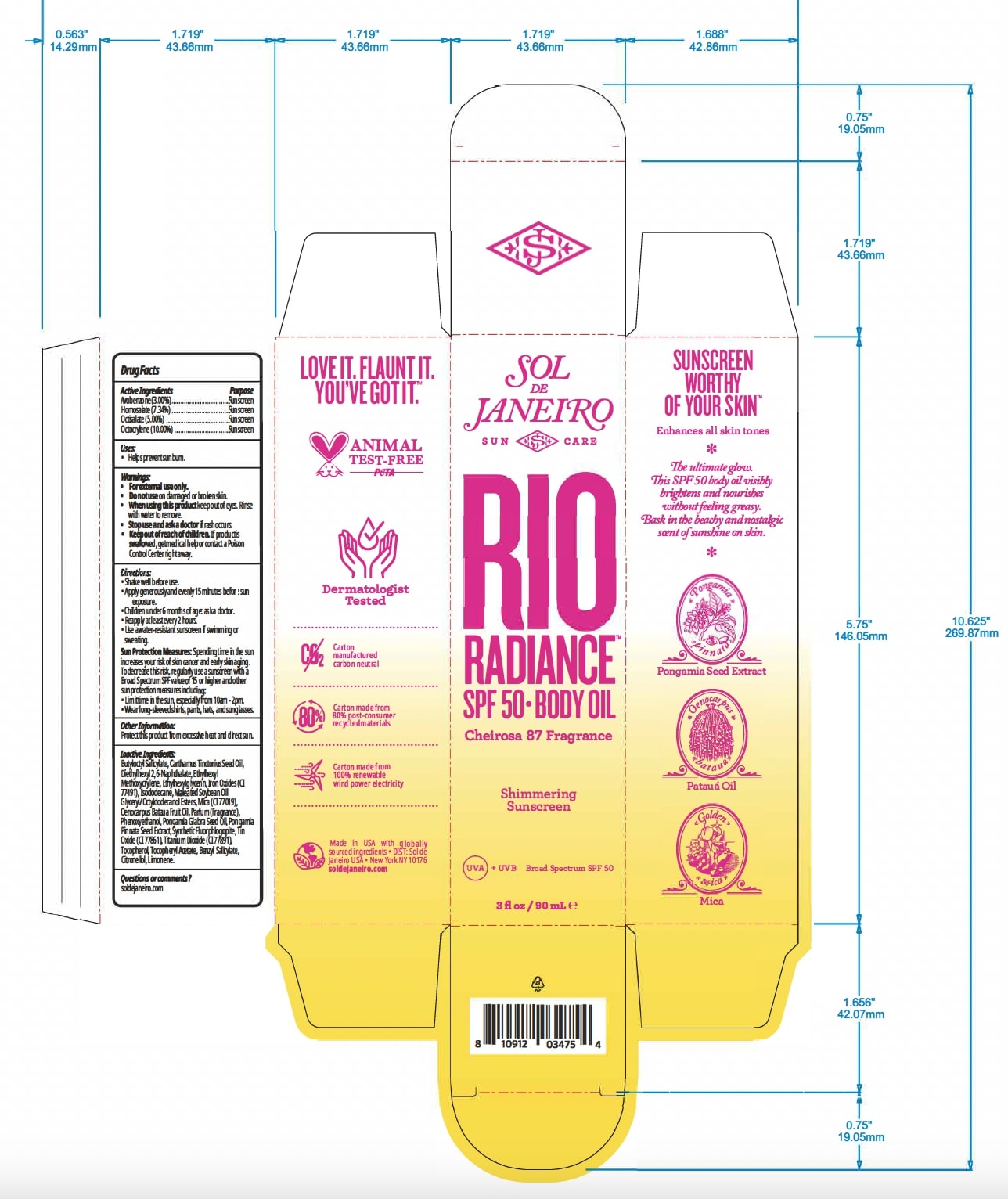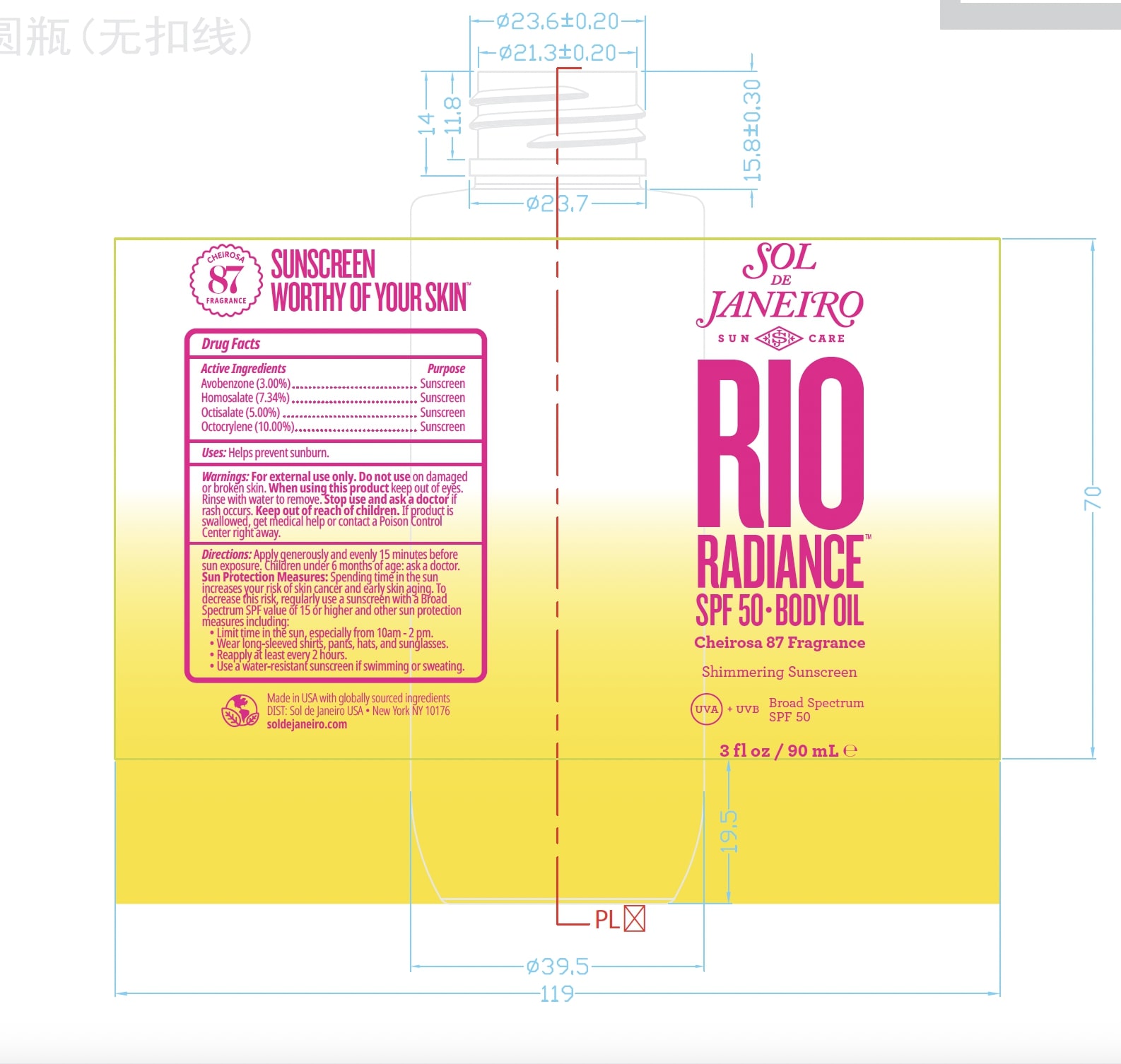 DRUG LABEL: Rio Radiance SPF 50 Body Oil
NDC: 83982-4837 | Form: OIL
Manufacturer: SOL DE JANEIRO USA, INC.
Category: otc | Type: HUMAN OTC DRUG LABEL
Date: 20240327

ACTIVE INGREDIENTS: OCTISALATE 50 mg/1 mL; AVOBENZONE 30 mg/1 mL; HOMOSALATE 77.4 mg/1 mL; OCTOCRYLENE 100 mg/1 mL
INACTIVE INGREDIENTS: SAFFLOWER OIL; PONGAMIA PINNATA SEED; ISODODECANE; BUTYLOCTYL SALICYLATE; DIETHYLHEXYL 2,6-NAPHTHALATE; OENOCARPUS BATAUA FRUIT OIL; TITANIUM DIOXIDE; FERRIC OXIDE RED; PHENOXYETHANOL; MAGNESIUM POTASSIUM ALUMINOSILICATE FLUORIDE; ALPHA-TOCOPHEROL ACETATE; ETHYLHEXYLGLYCERIN; ETHYLHEXYL METHOXYCRYLENE; KARUM SEED OIL; MICA; STANNOUS OXIDE; TOCOPHEROL

Drug Facts

Active Ingredients Purpose

Avobenzone (3.00%)....Sunscreen

Homosalate (7.34%).....Sunscreen

Octisalate (5.00%)........Sunscreen

Octocrylene (10.00%)..Sunscreen

Warnings:

• For extemal use only.
• Do not use on damaged or broken skin.
• When using this product keep our of eyes. Rinse
with water to remove.
• Stop use and ask a doctor if rash occurs.
• Keep out of reach of children. If product is swallowed, get medical help or contact a Poison Control Center right away.

Sun Protection Measures: Spending time in the sun increases

your risk of skin cancer and early skin aging. To decrease this risk,

regularly use a sunscreen with a Broad Spectrum SPF value of 15 or

higher and other sun protection measures including:

• Limit time in the sun, especially from 10am - 2pm.

• Wear long-sleeved shirts, pants, hats, and sunglasses.

Questions or comments?
soldejaneiro.com

Dosage: Evenly and generously apply to skin.

Administration: Topical

INACTIVE INGREDIENT

Butyloctyl Salicylate, Carthamus Tinctorius Seed Oil, Diethylhexyl 2,6-Naphthalate, Ethylhexyl Methoxycrylene, Ethylhexylglycerin, Iron Oxides (CI 77491), Isododecane, Maleated Soybean Oil Glyceryl/Octyldodecanol Esters, Mica (CI 77019), Oenocarpus Bataua Fruit Oil, Parfum (Fragrance), Phenoxyethanol, Pongamia Glabra Seed Oil, Pongamia Pinnata Seed Extract, Synthetic Fluorphlogopite, Tin Oxide (CI 77861), Titanium Dioxide (CI 77891), Tocopherol, Tocopheryl Acetate, Benzyl Salicylate, Citronellol, Limonene.

Uses:

• Helps prevent sunburn.

Directions:

• Apply generously and evenly 15 minutes before sun exposure.
• Children under 6 months of age: ask a doctor.
• Reapply at least every 2 hours.
• Use a water-resistant sunscreen if swimming or sweating.

Keep out of reach of children.

PURPOSE

Sunscreen